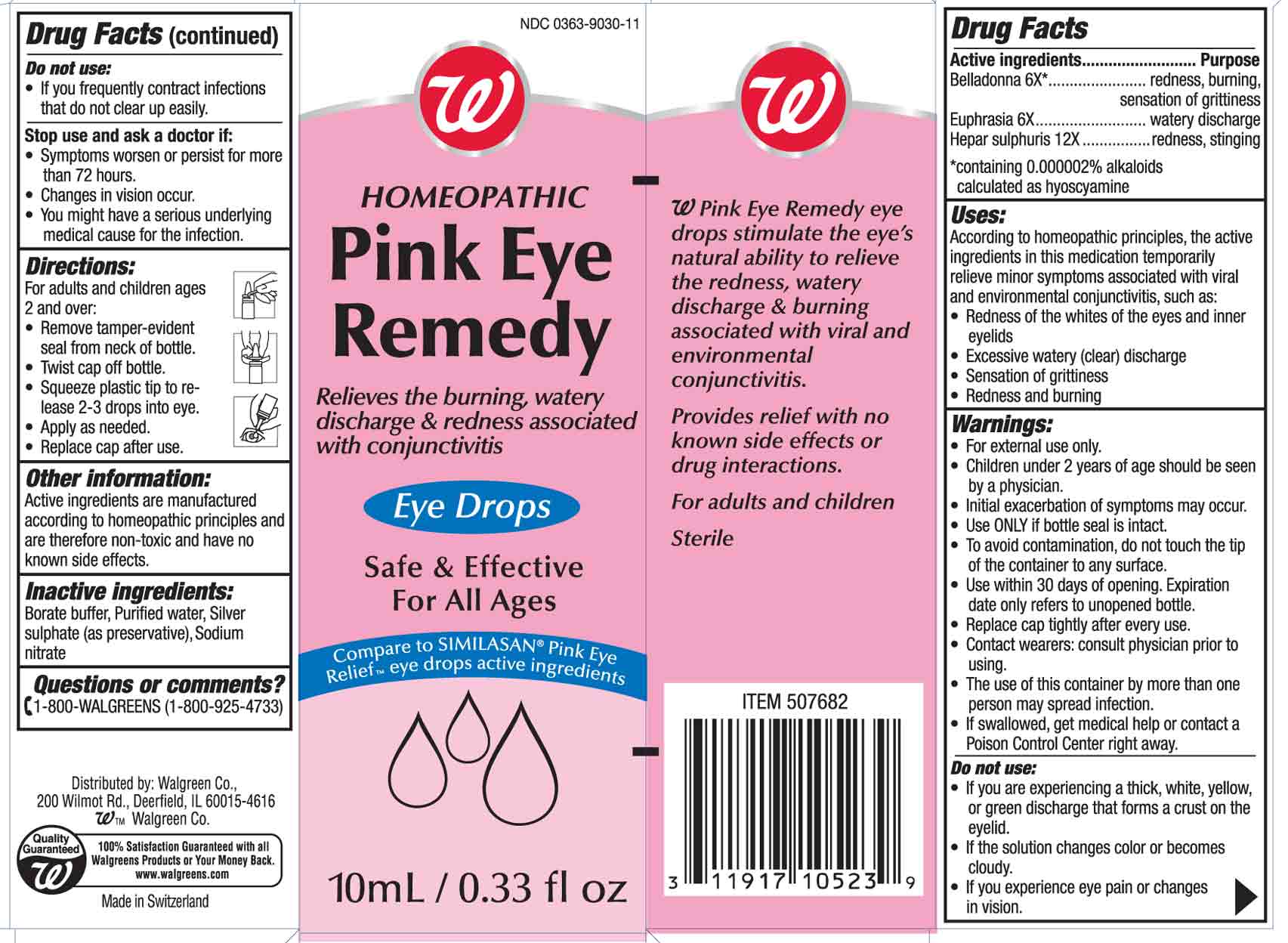 DRUG LABEL: Pink Eye Remedy
NDC: 0363-9030 | Form: SOLUTION/ DROPS
Manufacturer: Walgreen Co
Category: homeopathic | Type: HUMAN OTC DRUG LABEL
Date: 20100813

ACTIVE INGREDIENTS: ATROPA BELLADONNA 6 [hp_X]/10 mL; EUPHRASIA STRICTA 6 [hp_X]/10 mL; CALCIUM SULFIDE 12 [hp_X]/10 mL
INACTIVE INGREDIENTS: BORIC ACID; WATER; SILVER SULFATE; SODIUM NITRATE

Walgreens Pink Eye Remedy

Active Ingredient

Belladonna 6X*

ACTIVE INGREDIENT

Enter section text here

*containing 0.000002% alkaloids calculated as hyoscyamine

Purpose

redness, burning, sensation of grittiness

Active Ingredient

Euphrasia 6X

Purpose

watery discharge

Active Ingredient

Hepar sulphuris 12X

Purpose

redness, stinging

Uses

According to homeopathic principles, the active ingredients in this medication temporarily relieve minor symptoms associated with viral and environmental conjunctivitis such as:
- redness of the whites of the eyes and inner eyelids
- excessive watery (clear) discharge
- sensation of grittiness
- redness and burning

Warnings

- For external use only.
- Children under 2 years of age should be seen by a physician.
- Initial exacerbation of symptoms may occur.
- Use only if bottle seal is intact.
- To avoid contamination, do not touch the tip of the container to any surface.
- Use within 30 days of opening. Expiration date only refers to unopened bottle.
- Replace cap tightly after every use.
- Contact wearers: consult a physician prior to using.
- The use of this container by more than one person may spread infection.
- Keep this and all medicines out of the reach of children
- If swallowed, get medical help or contact a Poison Control Center right away.

Do Not Use

- if you are experiencing a think, white, yellow, or green discharge that forms a crust on the eyelid
- if the solution changes color or becomes cloudy
- if you experience eye pain or changes in vision
- if you frequently contract infections that do not clear up easily

Stop use and ask a doctor if

- symptoms worsen or persist for more than 72 hours
- changes in vision occur
- you might have a serious underlying medical cause for the infection

Directions

For adults and children ages 2 and over:
- remove tamper-evident seal from neck of bottle
- twist cap off bottle
- squeeze plastic tip to release 2-3 drops into eye
- apply as needed
- replace cap after use

Other Information

Active ingredients are manufactured according to homeopathic principles and are therefore non-toxic and have no known side effects.

Inactive ingredients

Borate buffer, Purified water, Silver sulphate (as preservative), Sodium nitrate

Questions?

Questions or Comments?
1-800-Walgreens (1-800-925-4733)

Prinicipal Display Panel

NDC 0363-9030-11
W
Homeopathic
Pink Eye Remedy
Eye Drops
10mL/ 0.33 fl oz

Walgreens Pink Eye Remedy box